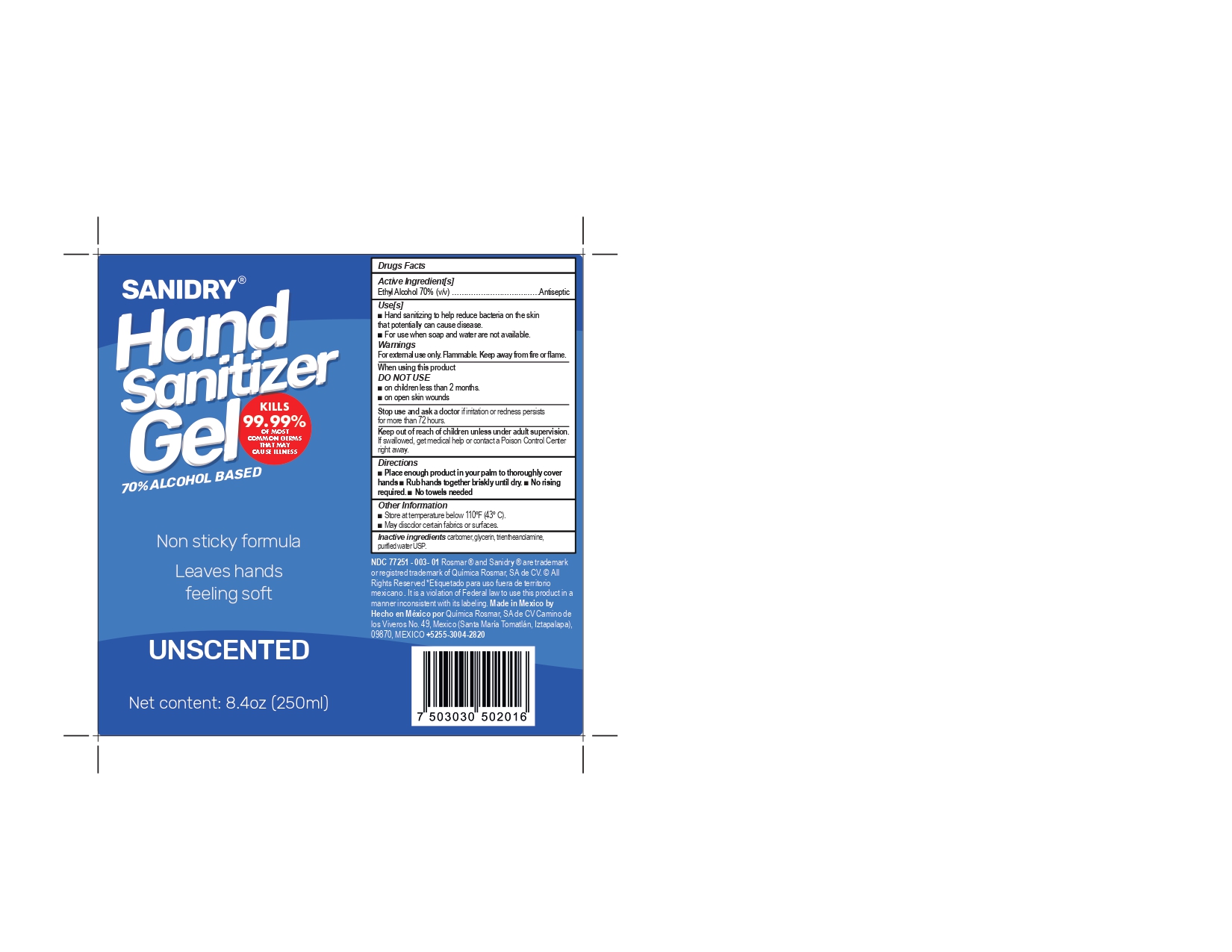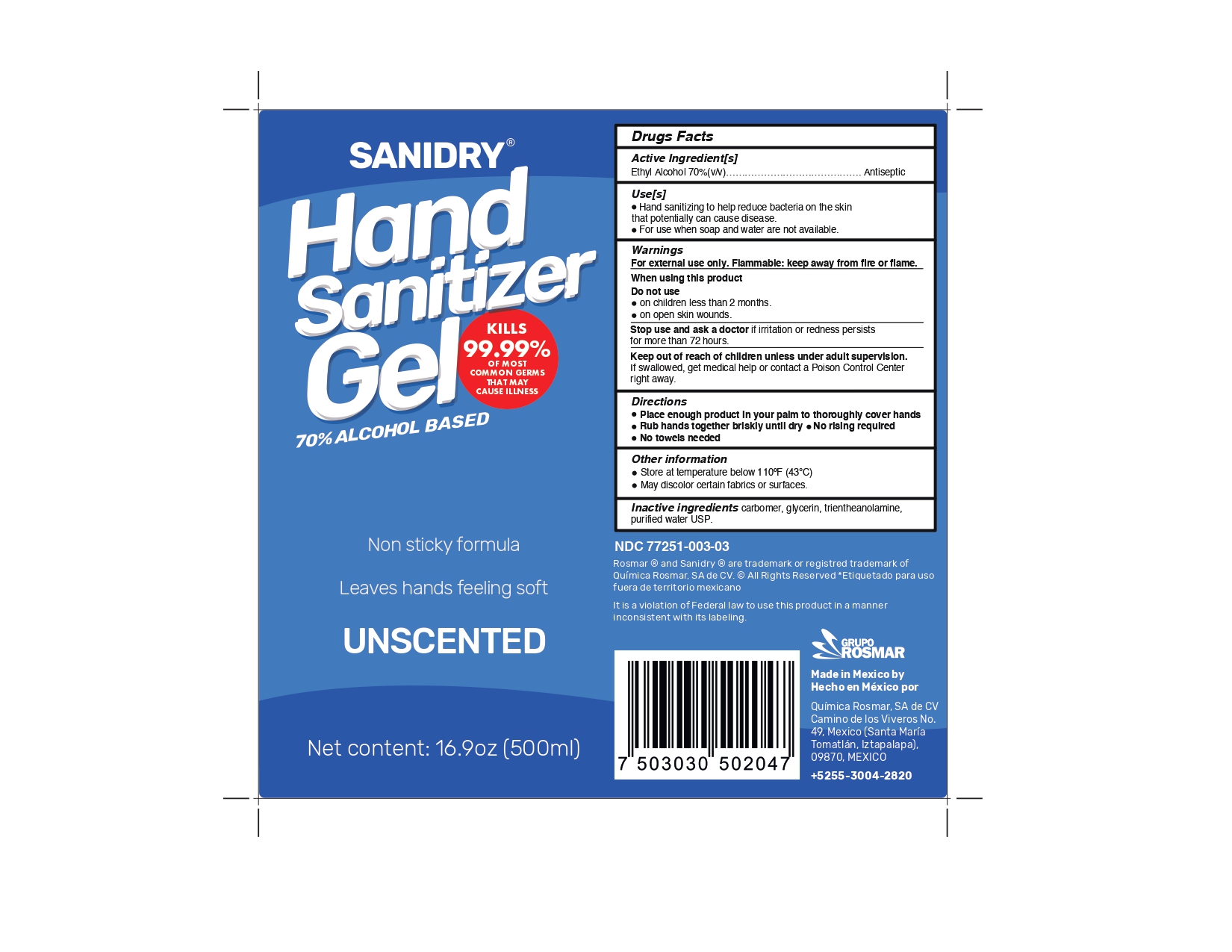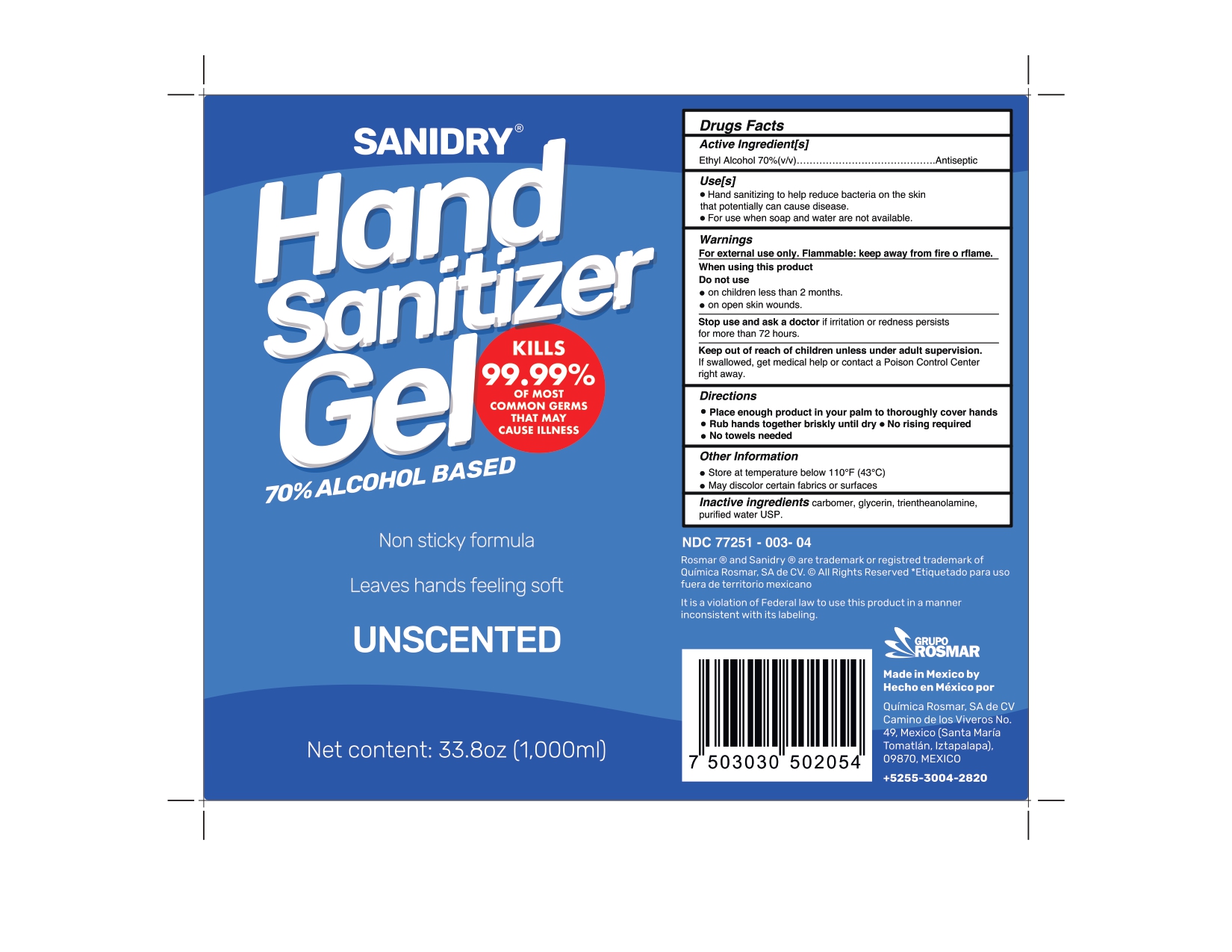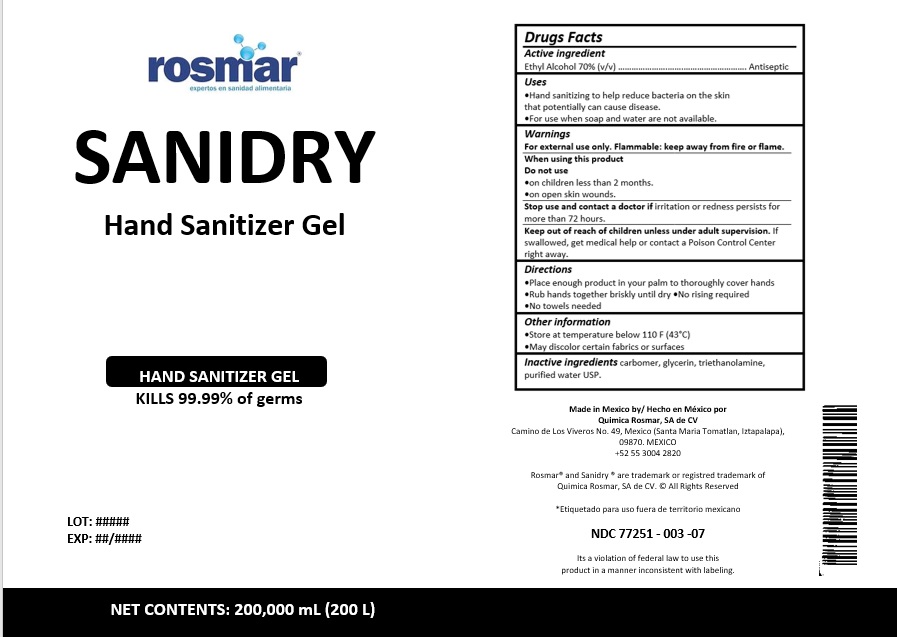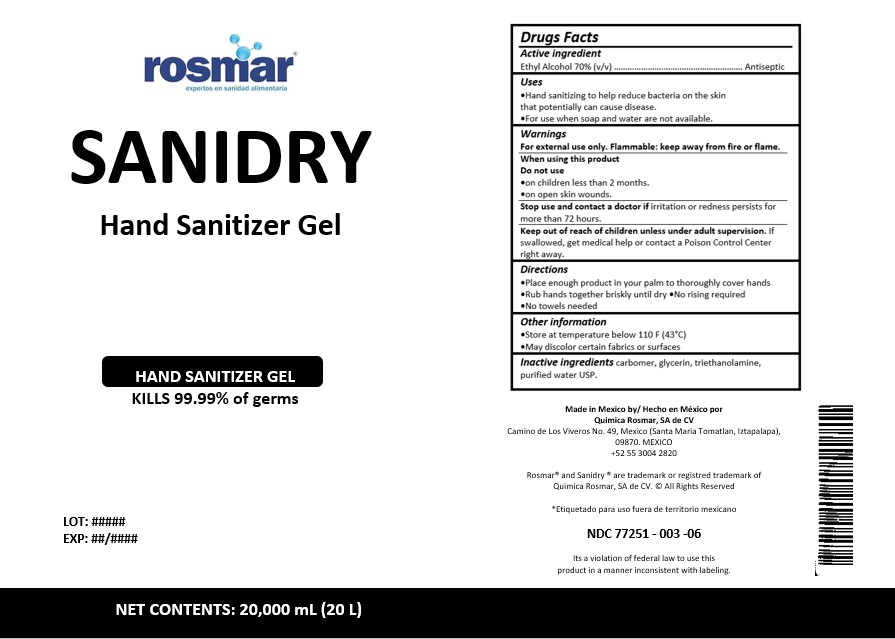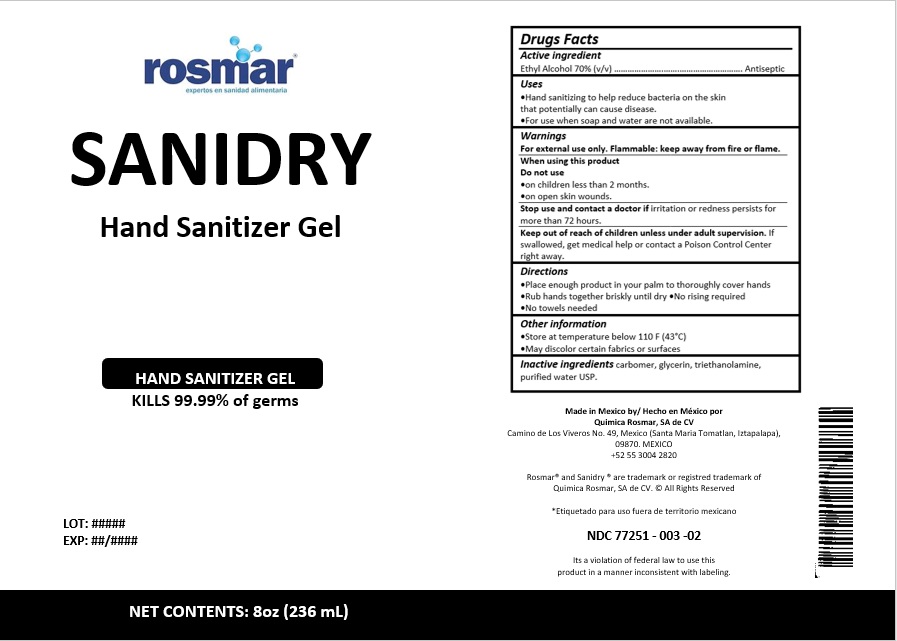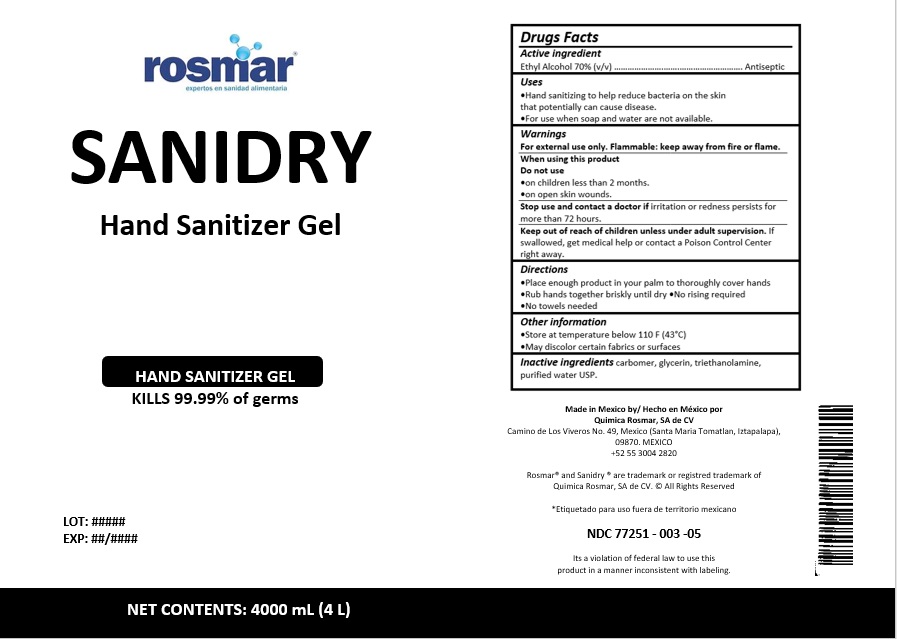 DRUG LABEL: Sanidry
NDC: 77251-003 | Form: GEL
Manufacturer: QUIMICA ROSMAR S.A. DE C.V.
Category: otc | Type: HUMAN OTC DRUG LABEL
Date: 20201207

ACTIVE INGREDIENTS: ALCOHOL 70 L/100 L
INACTIVE INGREDIENTS: CARBOMER HOMOPOLYMER, UNSPECIFIED TYPE; GLYCERIN; TROLAMINE; WATER

77251-003 Sanidry Hand Sanitizer

Active ingredient

Ethyl Alcohol 70% (v/v)

Purpose

Antiseptic

Uses

- Hand sanitizing to help reduce bacteria on the skin that potentially can cause disease.
- For use when soap and water are not available

Warnings

For external use only. Flammable: keep away from fire or flame.

When using this product

Do not use

- on children less than 2 months.
- on open skin wounds.

Stop use and ask a doctor if

irritation or redness persists for more than 72 hours

Keep out of reach of children unless under adult supervision

If swallowed, get medical help or contact a Poison Control Center right away.

Directions

- Place enough product in your palm to thoroughly cover hands
- Rub hands together briskly until dry
- No rinsing required
- No towels needed

Other information

- Store at temperature below 110 F (43°C)
- May discolor certain fabrics or surfaces

Inactive ingredients

carbomer, glycerin, triethanolamine, purified water USP.

PACKAGE LABEL

250 mL - NDC 77251-003-01

236 mL - NDC 77251-003-02

500 mL - NDC 77251-003-03

1000 mL - NDC 77251-003-04

4000 mL - NDC 77251-003-05

20 L - NDC 77251-003-06

200 L- NDC 77251-003-07